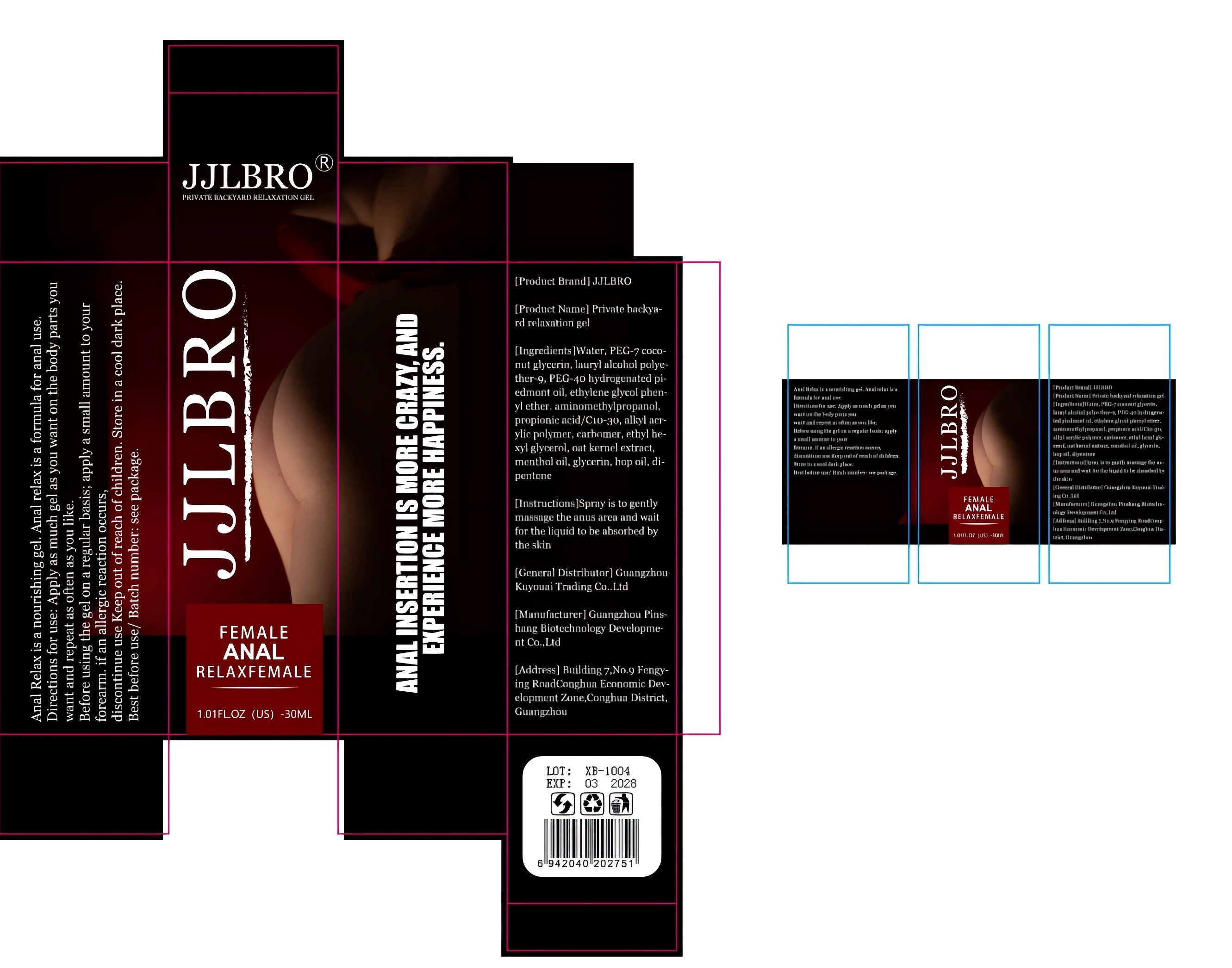 DRUG LABEL: Private backya-rd relaxation gel
NDC: 84372-057 | Form: GEL
Manufacturer: Shenzhen Zhumeng Times Technology Co., Ltd.
Category: otc | Type: HUMAN OTC DRUG LABEL
Date: 20240915

ACTIVE INGREDIENTS: LAURYL ALCOHOL 5 mg/5 mg
INACTIVE INGREDIENTS: POLYETHYLENE GLYCOL 3350; WATER; ALKYLSEVIN; MENTHOL, (+)-; PROPIONIC ACID; HOPS OIL; N-ETHYLHEXEDRONE; OAT; GLYCERIN; PHENOXYETHANOL; HYDROGENATED RAPESEED OIL; AMINOMETHYLPROPANOL; CARBOMER HOMOPOLYMER, UNSPECIFIED TYPE; 2-PENTENE

Active ingredients

lauryl alcohol polye-ther-9 5%

Purpose

Loose anal muscles

Uses

Apply around the anus and wait 5 minutes

Contraindications, Precautions, Warnings, and Instructions

Prohibit ingestion by mouth.

Do not put into eyes or ears.

No contact with wounds.

Dosage and administration

For external use only.

Do not use

Skin irritation occurs, wash with water, discontinue use

If symptoms do not improve, seek medical attention immediately

When using section

Skin irritation occurs, wash with water, discontinue use

If symptoms do not improve, seek medical attention immediately。

Allow 5 minutes for the product to take effect

Inactive ingredients

Water,PEG-7 coco-nut glycerin,PEG-4o hydrogenated pi-edmont oil,ethylene glycol phenyl ether,aminomethylpropanol,propionic acid/C10-30,alkyl acr-ylic polymer,carbomer,ethyl he-xyl glycerol,oat kernel extract,menthol oil,glycerin,hop oil,di-pentene

stop use

Wound breaks

Keep out of reach of children.

If sxralowed, get medical help or contact a Poison Conirol Cenler ngiht away.

RECENT MAJOR CHANGES

Package